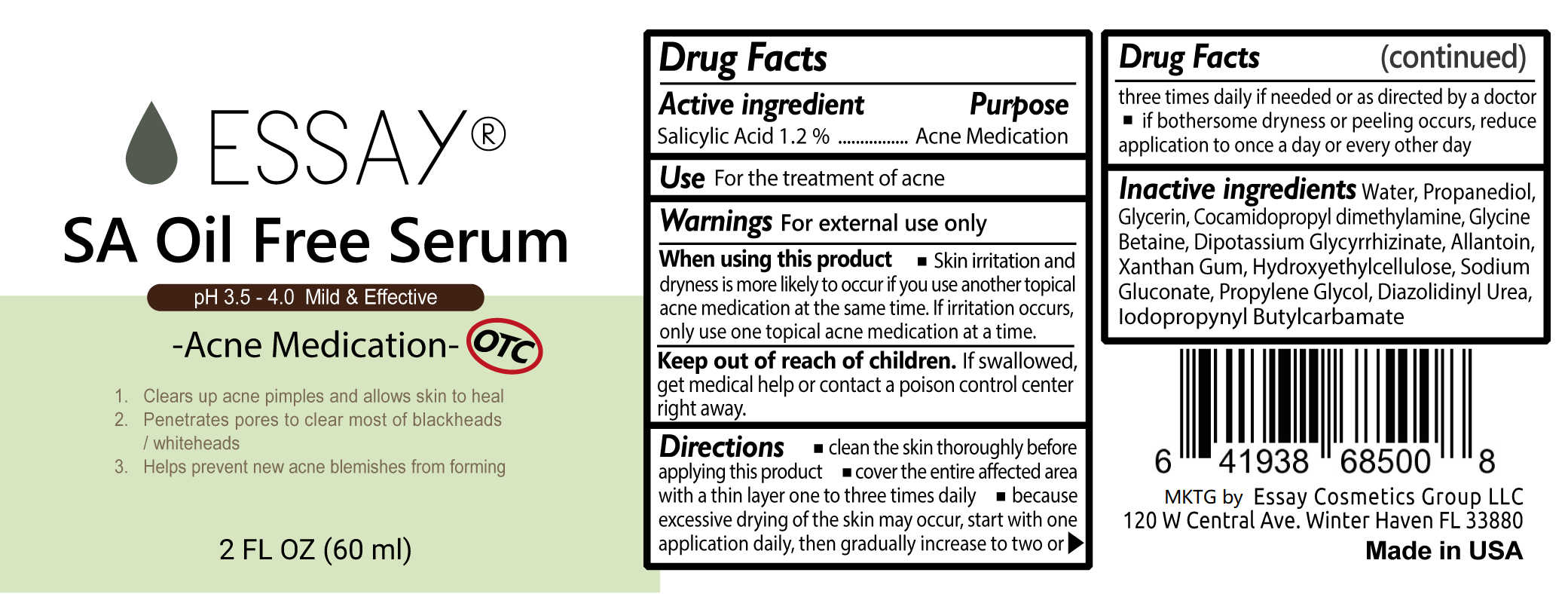 DRUG LABEL: SA Oil Free Serum
NDC: 72900-008 | Form: GEL
Manufacturer: Essay Cosmetics Group, LLC
Category: otc | Type: HUMAN OTC DRUG LABEL
Date: 20190326

ACTIVE INGREDIENTS: SALICYLIC ACID 0.72 g/0.72 g
INACTIVE INGREDIENTS: PROPYLENE GLYCOL; IODOPROPYNYL BUTYLCARBAMATE; WATER; GLYCERIN; COCAMIDOPROPYL DIMETHYLAMINE; SODIUM GLUCONATE; DIAZOLIDINYL UREA; BETAINE; GLYCYRRHIZINATE DIPOTASSIUM; PROPANEDIOL; ALLANTOIN; XANTHAN GUM; HYDROXYETHYL CELLULOSE (2000 CPS AT 1%)

SA Oil Free Serum-Essay

Active Ingredient

Active Ingredient 1.2% Salicylic Acid

Purpose

Acne Medication

INDICATIONS AND USAGE

■ apply evenly to the affected area one to two times daily

Directions

■ clean the skin thoroughly before applying this product ■ cover the entire affected area with a thin layer one to three times daily ■ because excessive drying of the skin may occur, start with one application daily, then gradually increase to two or three times daily if needed or as directed by a doctor ■ if bothersome dryness or peeling occurs, reduce application to once a day or every other day.

Inactive ingredients

Inactive ingredients Water, PEG-7 Glyceryl Cocoate, Propanediol, Glycerin, PEG-40 Hydrogenated Castor Oil, Cocamidopropyl dimethylamine, Glycine Betaine, Dipotassium Glycyrrhizinate, Bisabolol, Allantoin, Xanthan Gum, Hydroxyethylcellulose, Sodium Gluconate, Propylene Glycol, Diazolidinyl Urea, Lodopropynyl Butylcarbamate, Sodium Hydroxide

KEEP OUT OF REACH OF CHILDREN

If swallowed, get medical help or contact a Poison Control Center immediately.

Directions

■ clean the skin thoroughly before applying this product ■ cover the entire affected area with a thin layer one to three times daily ■ because excessive drying of the skin may occur, start with one application daily, then gradually increase to two or three times daily if needed or as directed by a doctor ■ if bothersome dryness or pealing occurs, reduce application to once a day or every other day

WARNINGS

Warnings ■ skin irritation and dryness is more likely to occur if you use another topical acne medication at the same time ■ if irritation occurs, only use one topical acne medication at a time

.